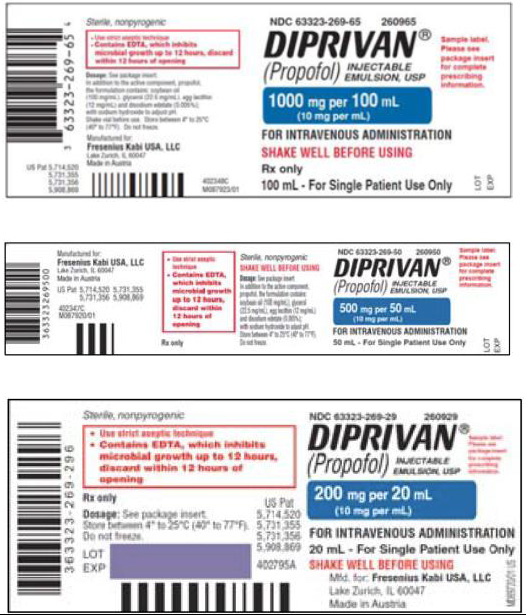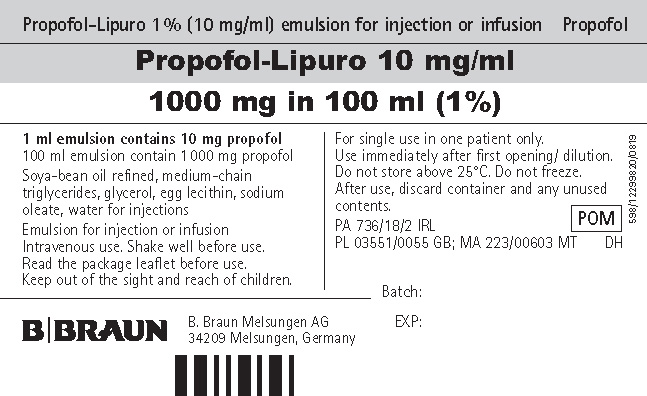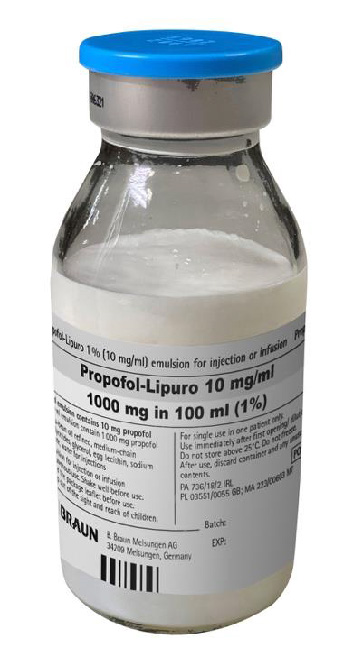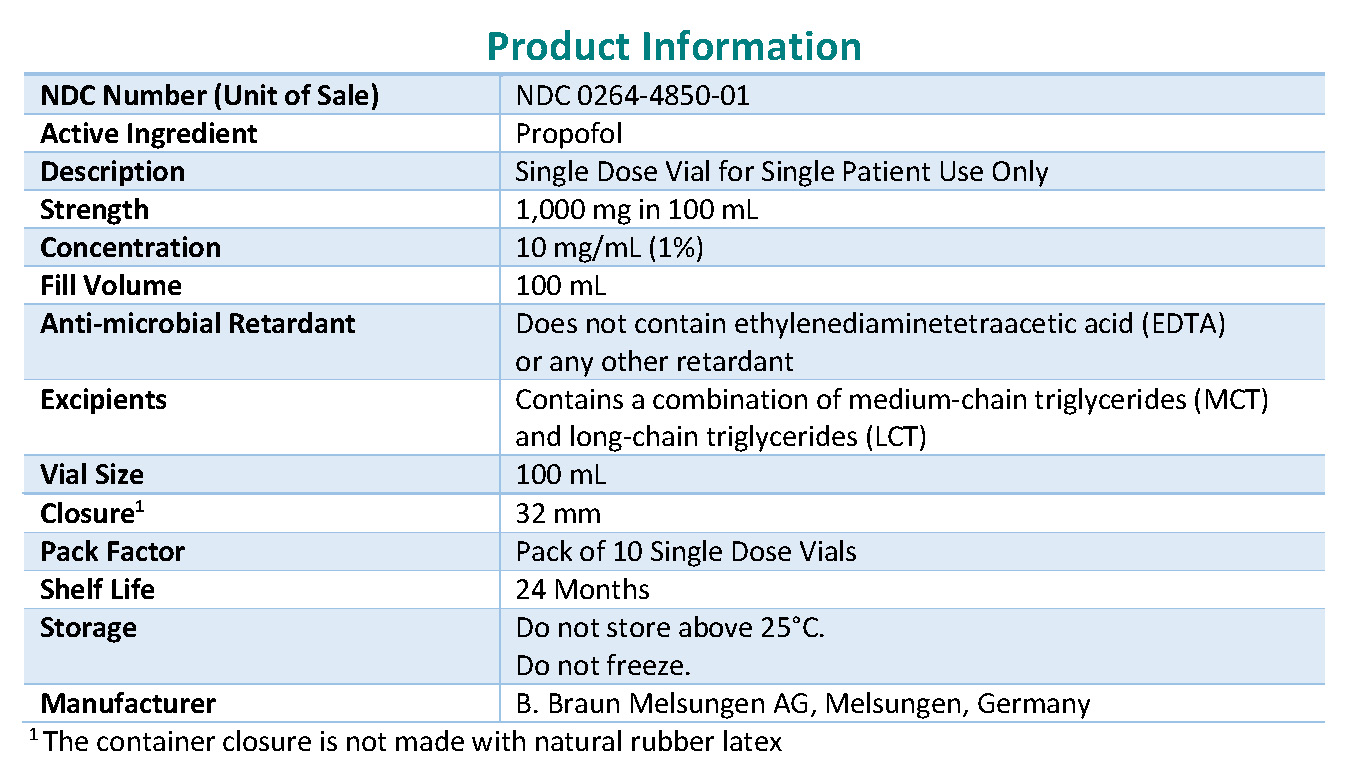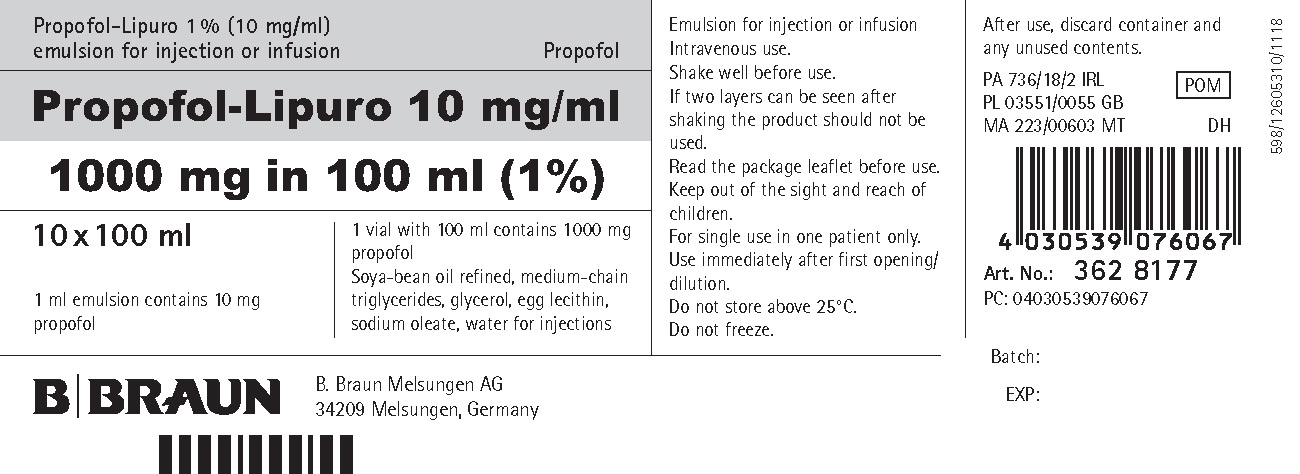 DRUG LABEL: Propofol Lipuro
NDC: 0264-4850 | Form: INJECTION, EMULSION
Manufacturer: B. Braun Medical Inc.
Category: prescription | Type: HUMAN PRESCRIPTION DRUG LABEL
Date: 20211220

ACTIVE INGREDIENTS: PROPOFOL 10 mg/1 mL
INACTIVE INGREDIENTS: MEDIUM-CHAIN TRIGLYCERIDES; SODIUM OLEATE; WATER; SOYBEAN OIL; GLYCERIN; EGG PHOSPHOLIPIDS

Propofol-Lipuro

FACT SHEET FOR HEALTH CARE PROVIDERS

EMERGENCY USE AUTHORIZATION (EUA) OF PROPOFOL-LIPURO 1%

INJECTABLE EMULSION FOR INFUSION

The U.S. Food and Drug Administration (FDA) has issued an Emergency Use Authorization (EUA) to permit the emergency use of the unapproved product, Propofol-Lipuro 1% injectable emulsion for infusion in 100 mL to maintain sedation via continuous infusion in patients greater than 16 years old who require mechanical ventilation in an intensive care unit (ICU) setting.

Propofol-Lipuro 1% injectable emulsion for infusion is not an FDA-approved drug in the United States. However, FDA has issued an EUA permitting the emergency use of Propofol-Lipuro 1% injectable emulsion for infusion during the COVID-19 pandemic and related shortage of propofol drug product.

Propofol-Lipuro 1% injectable emulsion for infusion is authorized only for the duration of the declaration that circumstances exist justifying the authorization of the emergency use under Section 564(b)(1) of the Act, 21 U.S.C. § 360bbb-3-(b)(1), unless the authorization is terminated or revoked sooner.

The scope of the EUA is limited as follows:

- Propofol-Lipuro 1% injectable emulsion for infusion will be used only to maintain sedation via continuous infusion in patients greater than 16 years old who require mechanical ventilation.
- Propofol-Lipuro 1% injectable emulsion for infusion will be administered only by a licensed healthcare provider in an ICU setting.
- Propofol-Lipuro 1% injectable emulsion for infusion will NOT be administered to pregnant women, unless there are no FDA-approved products available to maintain sedation for these patients should they require mechanical ventilation in an ICU setting.
- Propofol-Lipuro 1% injectable emulsion for infusion will be used only in accordance with the dosing regimens as detailed in the authorized Fact Sheets.

Product Description

Consistent with the EUA, B. Braun Melsungen AG, Germany, will offer the following presentations of Propofol-Lipuro 1% Emulsion.

Product Name And Description | MCT/LCT Concentration | Source/Type of Oil | Size | National Drug Code (NDC)
Propofol-Lipuro 1 % injectable emulsion for infusion 1,000 mg in 100 mL (propofol 10 mg per mL) | Medium Chain Triglycerides (MCT) 50 mg/mL; Long Chain Triglycerides (LCT) 50 mg/mL | Soybean oil, refined; medium-chain triglycerides | 100 mL | NDC 0264-4850-01

Propofol-Lipuro 1% injectable emulsion for infusion is approved in Europe as well as in many other international countries.

Propofol-Lipuro 1% injectable emulsion for infusion will be manufactured by B. Braun facilities in Germany as Propofol-Lipuro 1% Emulsion supplied in all other countries worldwide. The B. Braun’s manufacturing sites are inspected regularly by German and other National Competent Authorities confirming the fulfillment of good manufacturing practices (GMP) and other current standards. The manufacturing site in Melsungen, Germany was previously inspected by FDA.

Key Differences between FDA-approved Diprivan (propofol) Injectable Emulsion, USP Products and Propofol-Lipuro 1% (Propofol) injectable emulsion for infusion
 | Diprivan (propofol) Injectable Emulsion, USP Propofol 1,000 mg per 100 mL (10 mg per mL) | Propofol-Lipuro 1%(propofol) injectable emulsion for infusion 1,000 mg in 100 mL (10 mg/mL) | What does this mean to you as a healthcare professional?
Composition | Contains long-chain triglycerides (LCT) | Contains a combination of medium-chain triglycerides (MCT) and long-chain triglycerides (LCT) | Prolonged IV infusion of MCT to pregnant rabbits has been reported in the published literature to increase the RISK OF NEURAL TUBE DEFECTS.; Because it is not yet clear if there is differential risk for adverse developmental effects with Propofol-Lipuro 1% compared to Diprivan (propofol), Propofol-Lipuro 1% SHOULD NOT BE USED IN PREGNANT WOMEN unless there are no FDA-approved products available to maintain sedation in these patients who require mechanical ventilation in an ICU setting.
Indication | General anesthesia, procedural sedation, ICU sedation | ICU sedation ONLY | Propofol-Lipuro 1% is only to maintain sedation via continuous infusion in patients greater than 16 years old who require mechanical ventilation in the ICU setting.
Patient Population | Greater than 3 years old (procedural sedation and general anesthesia) Greater than 16 years old (ICU sedation) | Greater than 16 years old (ICU sedation) | Propofol-Lipuro 1% is only indicated to maintain sedation via continuous infusion for patients greater than 16 years old who require mechanical ventilation in the ICU setting.; Propofol-Lipuro 1% should not be used in pregnant women unless there are no FDA-approved products available to maintain sedation for these patients who require mechanical ventilation in an ICU setting.
Dosing | See package insert* | Administration rates of 0.3 to 4.0 mg propofol/kg bodyweight/h have been demonstrated to provide adequate sedation | Infusion rates greater than 4.0 mg propofol/kg bodyweight/h are not recommended due to risk of Propofol Infusion Syndrome.; The duration of administration must not exceed 7 days.
Method of Administration | Bolus or infusion | Infusion ONLY | Propofol-Lipuro 1% should be administered undiluted intravenously by continuous infusion. DO NOT ADMINISTER PROPOFOL-LIPURO 1% VIA BOLUS INJECTION.; Containers should be shaken before use. If two layers can be seen after shaking, the emulsion should not be used.; Do not admix with other medicinal products. Co-administration of other medicinal products or fluids added to the Propofol-Lipuro 1% infusion line must occur close to the cannula site using a Y-piece connector or a three-way valve. Propofol-Lipuro 1% Emulsion must not be administered via a microbiological filter.
Other Special Patient Populations | See package insert* | Caution should be taken when treating patients with mitochondrial disease, epilepsy, and disorders of fat metabolism. | Patients with mitochondrial disease may be susceptible to exacerbations of their disorder when undergoing ICU care. Maintenance of normothermia, provision of carbohydrates and good hydration are recommended for such patients. The early presentations of mitochondrial disease exacerbation and of the ‘propofol infusion syndrome’ may be similar.; Although several studies have demonstrated efficacy in treating status epilepticus, administration of propofol in epileptic patients may also increase the risk of seizure. Prior to administration of Propofol‐Lipuro 1%, antiepileptic medication(s) should be administered to patients with a history of medically managed seizures or when clinically indicated. For these patients, as well as for ARDS/respiratory failure and tetanus patients, sedation maintenance dosages were generally higher than those for other critically ill patient populations.; Appropriate care should be applied in patients with disorders of fat metabolism and in other conditions where lipid emulsions must be used cautiously. It is recommended that blood lipid levels should be monitored if propofol is administered to patients thought to be at particular risk of fat overload. Administration of propofol should be adjusted appropriately if the monitoring indicates that fat is being inadequately cleared from the body. If the patient is receiving other intravenous lipid concurrently, a reduction in quantity should be made in order to take account of the amount of lipid infused as part of the propofol formulation; 1.0 mL of Propofol-Lipuro 1 % Emulsion contains approximately 0.1 g of fat.
Drug interaction | See package insert* | Drug interaction with rifampicin, valproate | Profound hypotension has been reported following anesthetic induction with propofol in patients treated with rifampicin.; A need for lower propofol doses has been observed in patients taking valproate. When used concomitantly, a dose reduction of propofol may be considered.
Presence of antimicrobial retardant | Yes | NO | Propofol-Lipuro 1 % does NOT contain an antimicrobial retardant and supports growth of microorganisms.; STRICT ASEPTIC TECHNIQUE MUST ALWAYS BE MAINTAINED DURING HANDLING.; Each vial of Propofol-Lipuro 1 % is intended only for single administration for an individual patient. Vials are not intended for multiple use.; Propofol-Lipuro 1% must be drawn up aseptically into a sterile syringe or an infusion set immediately after breaking the vial seal. Administration must commence without delay. Asepsis must be maintained for both Propofol-Lipuro 1 % Emulsion and the infusion equipment throughout the infusion period.; The unused portion of a vial should be discarded immediately after opening. As with any propofol used in infusion, discard all product and infusion lines after 12 hours.
Contraindications | See package insert* | Propofol-Lipuro 1 % Emulsion should not be used in patients who are hypersensitive to peanut or soy | Propofol-Lipuro 1 % is contraindicated in patients with a known hypersensitivity to the active substance or to any of the excipients: soybean oil, refined; medium-chain triglycerides; glycerol; egg lecithin; sodium oleate; water for injections.; Propofol-Lipuro 1 % contains soya-bean oil and should not be used in patients who are hypersensitive to peanut or soy.
Bar code | Unit of use barcode on individual vials | No unit of use barcode | The barcode on the imported product label may not register accurately with the U.S. scanning systems. Institutions should manually input the imported product information into their systems and confirm that the barcode, if scanned, provides correct information. Alternative procedures should be followed to assure that the correct drug product is being used and administered to individual patients.

*Refer to https://www.accessdata.fda.gov/drugsatfda_docs/label/2017/019627s066lbl.pdf for the Diprivan package insert.

Please refer to the package insert for the full prescribing information of Propofol-Lipuro 1% injectable emulsion for infusion.

For questions regarding Propofol-Lipuro 1% injectable emulsion for infusion, please contact B. Braun Medical Inc.:

Company Name: B. Braun Medical Inc.
Address: 861 Marcon Blvd, Allentown, PA 18109
Country: United States
24-hour Telephone: +1 833-425-1464
E-Mail: productqualityexcellence@bbraunusa.com

What is an EUA

The United States FDA has made Propofol-Lipuro 1% injectable emulsion for infusion available to treat patients in an ICU during the COVID-19 pandemic under an emergency access mechanism called an Emergency Use Authorization (EUA). This EUA is supported by a Secretary of Health and Human Service (HHS) declaration that circumstances exist to justify the emergency use of drugs and biological products during the COVID-19 pandemic.

Propofol-Lipuro 1% injectable emulsion for infusion made available under an EUA has not undergone the same type of review as an FDA-approved product. FDA may issue an EUA when certain criteria are met, which includes that there are no adequate, approved, available alternatives. Based on the totality of scientific evidence available, it is reasonable to believe that Propofol-Lipuro 1% injectable emulsion for infusion has met certain criteria for safety, performance, and labeling and may be effective to maintain sedation via continuous infusion in patients greater than 16 years old who require mechanical ventilation in an ICU setting.

This EUA for Propofol-Lipuro 1% injectable emulsion for infusion is in effect for the duration of the COVID-19 declaration justifying emergency use of the product, unless terminated or revoked. The EUA will end when the declaration is terminated or revoked or when there is a change in the approval status of the product such that an EUA is no longer needed.

This communication and product information is available on the B. Braun Medical Inc. website https://www.bbraunusa.com/en/company/newsroom/covid19.html# as well as the FDA webpage which includes links to patient fact sheet.

Adverse Event Reporting

Healthcare facilities and prescribing healthcare providers or their designee receiving Propofol-Lipuro 1 % injectable emulsion for infusion will track all medication errors associated with the use of and all serious adverse events that are considered potentially attributable to Propofol-Lipuro 1% injectable emulsion for infusion.

Adverse events or quality problems experienced with the use of this product must also be reported to the FDA using one of the following methods:

- Complete and submit a MedWatch form online: www.fda.gov/medwatch/report.htm or
- Complete and submit FDA Form 3500 (health professional) by fax (1-800-FDA-0178) (this form can be found via link above).

Call 1-800-FDA-1088 for questions. Submitted reports should state, “Propofol-Lipuro 1% injectable emulsion for infusion use for COVID-19 under Emergency Use Authorization (EUA)” at the beginning of the question “Describe Event” for further analysis.

For questions regarding Propofol-Lipuro 1% (10 mg/mL) injectable emulsion for infusion for continuous infusion, please contact B. Braun Medical Inc.:

Company Name: B. Braun Medical Inc.
24-hour Telephone: +1 833-425-1464
E-Mail: productqualityexcellence@bbraunusa.com

Comparison Table of FDA-approved Diprivan (propofol) Injectable Emulsion, USP 10 mg/mL and
Propofol-Lipuro 1 % (10 mg/mL) injectable emulsion for infusion
Product Name | Diprivan (propofol) Injectable Emulsion, USP | Propofol-Lipuro 1 % injectable emulsion for infusion
Propofol concentration | 10 mg/mL | 10 mg/mL
Product labels 100 mL |  | Note: The imported product labels include that Propofol-Lipuro 1% is “for injection or infusion”. However, Propofol-Lipuro 1% is only authorized for use in the U.S. as “for infusion”.
Active Ingredient | Propofol | Propofol
Excipients | Soybean oil Glycerol Egg phospholipids Edetate disodium Sodium hydroxide | Soybean oil, refined Medium-chain triglycerides Egg phospholipids for injection Glycerol Sodium oleate Water for injection
Fill Volume | 20 mL 50 mL 100 mL | 100 mL
Duration | Drug holiday after 5 days to replace urine zinc losses | Do not administer for more than 7 days.
Dilution | Dilution to 2 mg/mL with; 5% Dextrose Injection only | Do Not Dilute.
Bolus | Bolus injection permitted | Infusion ONLY
Description | Single Dose Vial for Single Patient Use Only | Single Dose Vial for Single Patient Use Only
Company | Fresenius Kabi USA | B. Braun Melsungen AG Germany

Propofol-Lipuro 1% (propofol)

injectable emulsion for infusion

1,000 mg in 100 mL (10 mg/mL)

Propofol-Lipuro 1% (propofol) injectable emulsion for infusion 1,000 mg in 100 mL (10 mg/mL) contains the same active ingredient, strength, and concentration as Diprivan® (propofol) injectable emulsion for infusion USP 1,000 mg per 100 mL (10 mg per mL).

- Propofol-Lipuro 1% injectable emulsion for infusion is not FDA-approved
  - Propofol-Lipuro 1% injectable emulsion for infusion is approved in Europe, as well as many other international countries outside of the United States.
  - Propofol-Lipuro 1% injectable emulsion for infusion has been authorized by FDA for use under an Emergency Use Authorization (EUA)
  - Propofol-Lipuro 1% injectable emulsion for infusion is authorized only for the duration of the declaration that circumstances exist justifying the authorization of the emergency use under Section 564(b)(1) of the Act, 21 U.S.C. § 360bbb-3-(b)(1), unless the authorization is terminated or revoked sooner

To place an order, contact your local sales representative.

Fact Sheet for Patients, Parents, And Caregivers

Emergency Use Authorization (EUA) of PROPOFOL-LIPURO 1% (propofol)

INJECTABLE EMULSION FOR INFUSION

During CORONAVIRUS DISEASE 2019 (COVID-19) Pandemic

This fact sheet contains information to help you understand the risks and benefits of Propofol-Lipuro 1% (10 mg/mL) injectable emulsion for infusion that you have received or may receive.

There is currently a shortage of U.S. Food and Drug Administration (FDA)-approved propofol products that maintain sedation for patients who are on a machine that helps with breathing (ventilator) due to the COVID-19 pandemic. Propofol-Lipuro 1% injectable emulsion for infusion is not an FDA-approved medicine in the United States. Propofol-Lipuro 1% injectable emulsion for infusion contains the same active ingredient, propofol, at the same strength as Diprivan Injectable Emulsion and other propofol products approved in the United States. Propofol-Lipuro 1% injectable emulsion for infusion is currently approved in Europe and other international countries. Read this Fact Sheet for information about Propofol-Lipuro 1% injectable emulsion for infusion. Talk to your healthcare provider if you have questions. It is your choice to take Propofol-Lipuro 1% injectable emulsion for infusion or stop it at any time.

What is COVID-19?

COVID-19 is caused by a virus called a coronavirus. This type of coronavirus has not been seen before. This new coronavirus was first found in people in December 2019. You can get COVID-19 through contact with another person who has the virus.

COVID-19 illnesses have ranged from very mild (including some with no reported symptoms) to severe, including illness resulting in death. While information so far suggests that most COVID-19 illness is mild, serious illness can happen and may cause some of your other medical conditions to become worse. Older people and people of all ages with severe, long lasting (chronic) medical conditions like heart disease, lung disease, and diabetes, for example, seem to be at higher risk of being hospitalized for COVID-19.

The symptoms of COVID-19 are fever, cough and shortness of breath, which may appear 2 to 14 days after exposure. Serious illness including breathing problems can occur and may cause your other medical conditions to become worse.

What is PROPOFOL-LIPURO 1% INJECTABLE EMULSION FOR INFUSION?

Propofol-Lipuro 1% injectable emulsion for infusion belongs to a group of medicines called sedatives/hypnotics. It will be used to help calm (sedate) you if you need a tube inserted (intubation) and a machine to help you breathe (ventilator) while in an ICU.

What do I need to know before I receive PROPOFOL-LIPURO 1% INJECTABLE EMULSION FOR INFUSION?

Who should not receive Propofol-Lipuro 1% injectable emulsion for infusion?

Do not receive Propofol-Lipuro 1% injectable emulsion for infusion if:

- You have received propofol before and have had an allergic reaction to it
- You are allergic (hypersensitive) to soy, peanut, or any of the other ingredients of this medicine
- You are 16 years of age or younger

What should I tell my healthcare provider before I receive Propofol-Lipuro 1% injectable emulsion for infusion?

Please tell your healthcare provider about all of your medical conditions, including if you have:

- Serious head injuries
- Mitochondrial disease
- A disorder in which your body does not handle fat properly or any other health problems in which
  giving you fat emulsions may cause a health problem
- Dehydration (your blood volume is too low, or hypovolemia)
- Heart, kidney, or liver problems
- High pressure within your brain
- Problems with your breathing
- Epilepsy
- Are pregnant or plan to become pregnant.
- Are breastfeeding or plan to breastfeed
- Are taking any medicines, including prescription, over‐the‐counter, vitamins, or herbal products

Your healthcare provider will consider that other medicines with an inhibiting effect on the central nervous system may increase the effects of propofol when given together with propofol. Special care will be taken if you are also receiving an antibiotic containing rifampicin or an anti-seizure medication containing valproate.

How will I receive PROPOFOL-LIPURO 1% INJECTABLE EMULSION FOR INFUSION?

Propofol-Lipuro 1% injectable emulsion for infusion is given to you through a vein (IV) under the direct supervision of an anesthesiologist or intensive care doctor who will closely control the amount of Propofol-Lipuro 1% injectable emulsion given to you.

Dosage

The dose you are given will vary depending on your age, body weight, and physical condition. The doctor will give the correct dose to achieve the required level of sedation, by carefully watching your responses and vital signs (pulse, blood pressure, breathing, etc).

Propofol-Lipuro 1% injectable emulsion will be given by infusion and only for a maximum of 7 days.

What are the important possible side effects of PROPOFOL-LIPURO 1% INJECTABLE EMULSION FOR INFUSION?

The most common side effects are:

- Pain at the injection site
- Drop in blood pressure
- Changes in heart rate
- Changes in breathing, coughing, and hiccups
- Headache, nausea, or vomiting during recovery from propofol sedation

Less common side effects are:

- Blood clots in veins or inflammation of veins at the injection site
- Seizures
- Fever
- Allergic reactions, which can include swelling of the face, tongue and/or throat, wheezing and/or
  difficulty breathing, skin redness, and low blood pressure
- Fluid on lungs (lung edema)
- Inflammation of the pancreas
- Loss of sexual control during the time of recovery
- Change in color of your urine after prolonged intravenous administration of propofol
- Skin or tissue damage if the medicine is accidentally injected outside of a vein
- Involuntary movements
- Mood changes
- Drug abuse and drug dependence
- Cardiac arrest, heart failure
- Shallow breathing
- Pain and/or swelling at the injection site after the medicine was accidentally injected outside of a
  vein

What other treatment choices are there?

Your anesthesiologist or intensive care doctor may give you other sedation agents depending on your medical condition.

What if I am pregnant or breastfeeding?

Tell your healthcare provider if you are pregnant, think you may be pregnant, or are planning to have a baby. Propofol-Lipuro 1% injectable emulsion for infusion may harm your unborn baby. Propofol-Lipuro 1% injectable emulsion for infusion should be used in pregnant women only if there are no other FDA-approved medicines available for your medical condition.

Propofol-Lipuro 1% injectable emulsion for infusion may pass into breast milk. You should stop breastfeeding and throw away (discard) breast milk for 24 hours after you have received Propofol-Lipuro 1% injectable emulsion for infusion.

How do I report side effects with PROPOFOL-LIPURO 1% INJECTABLE EMULSION FOR INFUSION?

Tell your healthcare provider right away if you have any side effect that bothers you or does not go away.

Report side effects to FDA MedWatch at www.fda.gov/medwatch or call 1-800-FDA-1088. You may also report the problem to the B. Braun Medical Inc. USA by phone at 1-833-425-1464 or by email at productqualityexcellence@bbraunusa.com.

HOW CAN I LEARN MORE ABOUT COVID-19?

- Ask your healthcare provider
- Visit https://www.cdc.gov/COVID19
- Contact your local or state public health department

WHAT IS AN EMERGENCY USE AUTHORIZATION (EUA)?

The United States FDA has made Propofol-Lipuro 1% injectable emulsion for infusion available under an emergency access mechanism called an EUA. The EUA is supported by a Secretary of Health and Human Service (HHS) declaration that circumstances exist to justify the emergency use of drugs and biological products during the COVID-19 pandemic.

Propofol-Lipuro 1% injectable emulsion for infusion has not undergone the same type of review as an FDA-approved product. FDA may issue an EUA when certain criteria are met, which includes that there are no adequate, approved, and available alternatives. In addition, the FDA decision is based on the totality of scientific evidence available showing that it is reasonable to believe that the product meets certain criteria for safety, performance, and labeling, and may be effective in treatment of patients during the COVID-19 pandemic. All of those criteria must be met to allow for the product to be used in the treatment of patients during the COVID-19 pandemic.

The EUA for Propofol-Lipuro 1% injectable emulsion for infusion is in effect for the duration of the COVID-19 declaration justifying emergency use of these products, unless terminated or revoked (after which the products may no longer be used).

PRINCIPAL DISPLAY PANEL - VIAL

Propofol-Lipuro 1 % (10 mg/ml) emulsion for injection or infusion

Propofol

Propofol-Lipuro 10 mg/ml
1000 mg in 100 ml (1%)

1 ml emulsion contains 10 mg propofol
100 ml emulsion contain 1 000 mg propofol

Soya-bean oil refined, medium-chain triglycerides, glycerol, egg lecithin, sodium oleate, water for injections

Emulsion for injection or infusion Intravenous use. Shake well before use. Read the package leaflet before use. Keep out of the sight and reach of children.

For single use in one patient only. Use immediately after first opening/ dilution. Do not store above 25°C. Do not freeze. After use, discard container and any unused contents.

PA 736/18/2 IRL

POM

PL 03551/0055 GB; MA 223/00603 MT DH

B. Braun Melsungen AG
34209 Melsungen, Germany

598/12299820/0819

Batch:

EXP:

PRINCIPAL DISPLAY PANEL - CARTON

Propofol-Lipuro 1 % (10 mg/ml)
emulsion for injection or infusion

Propofol

Propofol-Lipuro 10 mg/ml
1000 mg in 100 ml (1%)

10 x 100 ml

1 ml emulsion contains 10 mg propofol

1 vial with 100 ml contains 1 000 mg propofol
Soya-bean oil refined, medium-chain triglycerides, glycerol, egg lecithin, sodium oleate, water for injections

Emulsion for injection or infusion Intravenous use.
Shake well before use.
If two layers can be seen after shaking the product should not be used.
Read the package leaflet before use. Keep out of the sight and reach of children.
For single use in one patient only. Use immediately after first opening/ dilution.
Do not store above 25°C.
Do not freeze.

After use, discard container and any unused contents.

PA 736/18/2 IRL

PL 03551/0055 GB

MA 223/00603 MT DH

POM

Art. No.: 362 8177

PC: 04030539076067

B. Braun Melsungen AG
34209 Melsungen, Germany

598/12605310/1118

Batch:

EXP: